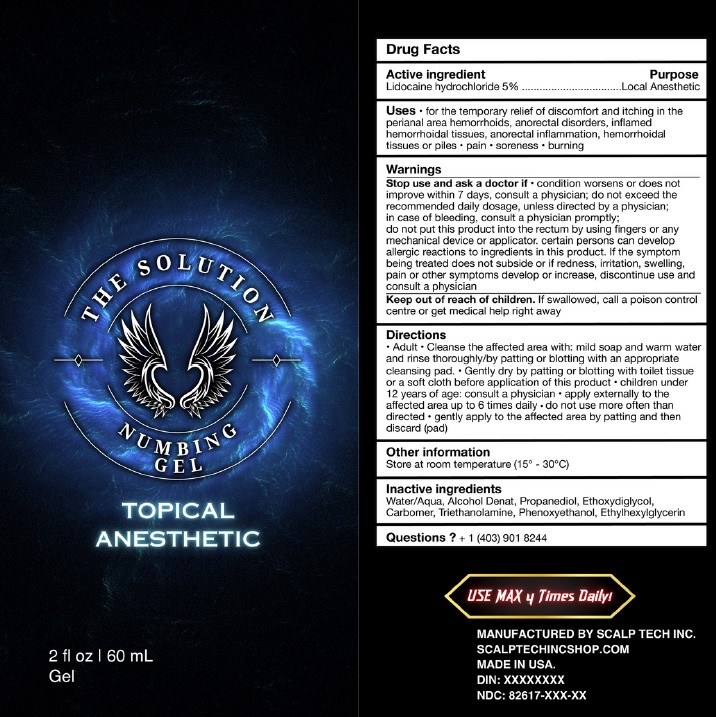 DRUG LABEL: THE SOLUTION NUMBING
NDC: 82617-105 | Form: GEL
Manufacturer: SCALP TECH INC
Category: otc | Type: HUMAN OTC DRUG LABEL
Date: 20240525

ACTIVE INGREDIENTS: LIDOCAINE HYDROCHLORIDE 5 g/100 mL
INACTIVE INGREDIENTS: TROLAMINE; ETHYLHEXYLGLYCERIN; ALCOHOL; DIETHYLENE GLYCOL MONOETHYL ETHER; WATER; ALLANTOIN; PROPANEDIOL; CARBOMER 934; PHENOXYETHANOL

SCALP TECH (as PLD) - THE SOLUTION NUMBING GEL (82617-105)

ACTIVE INGREDIENTS

LIDOCAINE HYDROCHLORIDE 5%

PURPOSE

LOCAL ANESTHETICS

USES

- FOR THE TEMPORARY RELIEF OF DISCOMFORT AND ITCHING IN THE PERIANAL AREA HEMORRHOIDS, ANORECTAL DISORDERS, INFLAMED HEMORRHOIDAL TISSUES, ANORECTAL INFLAMMATION, HEMORRHOIDAL TISSUES OR PILES
- PAIN
- SORENESS
- BURNING

WARNINGS

STOP USE AND ASK A DOCTOR IF

- CONDITION WORSENS OR DOES NOT IMPROVE WITHIN 7 DAYS, CONSULT A PHYSICIAN; DO NOT EXCEED THE RECOMMENDED DAILY DOSAGE, UNLESS DIRECTED BY A PHYSICIAN; IN CASE OF BLEEDING, CONSULT A PHYSICIAN PROMPTLY; DO NOT PUT THIS PRODUCT INTO THE RECTUM BY USING FINGERS OR ANY MECHANICAL DEVICE OR APPLICATOR. CERTAIN PERSONS CAN DEVELOP ALLERGIC REACTIONS TO INGREDIENTS IN THIS PRODUCT. IF THE SYMPTOM BEING TREATED DOES NOT SUBSIDE OR IF REDNESS, IRRITATION, SWELLING, PAIN OR OTHER SYMPTOMS DEVELOP OR INCREASE, DISCONTINUE USE AND CONSULT A PHYSICIAN.

KEEP OUT OF REACH OF CHILDREN. IF SWALLOWED, CALL A POISON CONTROL CENTRE OR GET MEDICAL HELP RIGHT AWAY.

DIRECTIONS

- ADULT
- CLEANSE THE AFFECTED AREA WITH: MILD SOAP AND WARM WATER AND RINSE THOROUGHLY/BY PATTING OR BLOTTING WITH AN APPROPRIATE CLEANSING PAD.
- GENTLY DRY BY PATTING OR BLOTTING WITH TOILET TISSUE OR A SOFT CLOTH BEFORE APPLICATION OF THIS PRODUCT
- CHILDREN UNDER 12 YEARS OF AGE: CONSULT A PHYSICIAN
- APPLY EXTERNALLY TO THE AFFECTED AREA UP TO 6 TIMES DAILY
- DO NOT USE MORE OFTEN THAN DIRECTED
- GENTLY APPLY TO THE AFFECTED AREA BY PATTING AND THEN DISCARD (PAD)

OTHER INFORMATION

STORE AT ROOM TEMPERATURE (15° - 30°C)

INACTIVE INGREDIENTS

WATER/AQUA, ALCOHOL DENAT, PROPANEDIOL, ETHOXYDIGLYCOL, CARBOMER, TRIETHANOLAMINE, PHENOXYETHANOL, ETHYLHEXYLGLYCERIN

QUESTIONS?

CALL - 1 (403) 901-8244